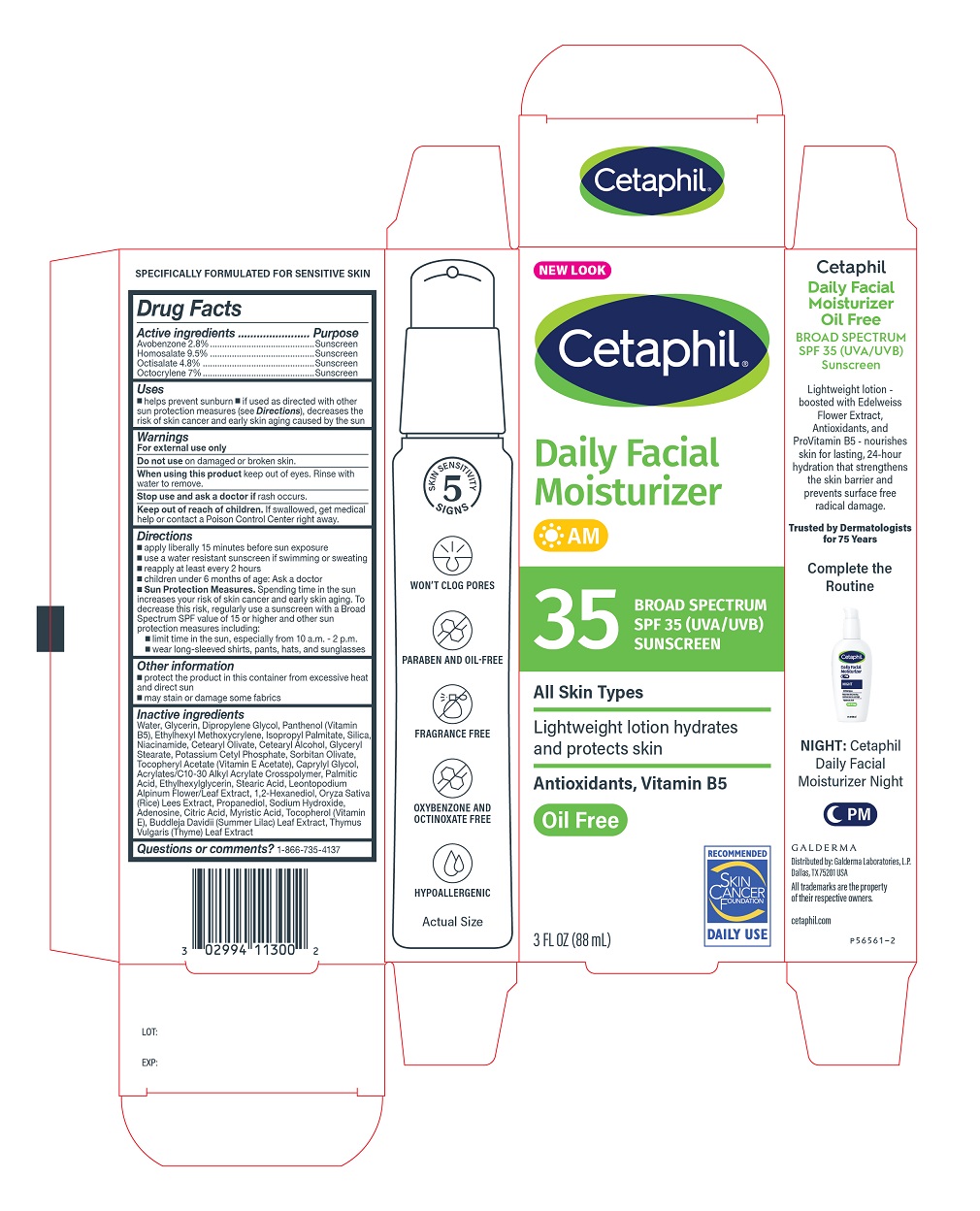 DRUG LABEL: Cetaphil Daily Facial Moisturizer with suncreen SPF 35
NDC: 0299-4113 | Form: LOTION
Manufacturer: Galderma Laboratories, L.P.
Category: otc | Type: HUMAN OTC DRUG LABEL
Date: 20231114

ACTIVE INGREDIENTS: Avobenzone 28 mg/1 mL; Homosalate 95 mg/1 mL; Octisalate 48 mg/1 mL; Octocrylene 70 mg/1 mL
INACTIVE INGREDIENTS: Water; Glycerin; Dipropylene Glycol; Panthenol; Ethylhexyl Methoxycrylene; Isopropyl Palmitate; Silicon Dioxide; Niacinamide; Cetearyl Olivate; Cetostearyl Alcohol; Glyceryl Monostearate; Potassium Cetyl Phosphate; Sorbitan Olivate; .Alpha.-Tocopherol Acetate; Caprylyl Glycol; Carbomer Interpolymer Type A (Allyl Sucrose Crosslinked); Palmitic Acid; Ethylhexylglycerin; Stearic Acid; Leontopodium Nivale Subsp. Alpinum Flowering Top; 1,2-Hexanediol; Rice Germ; Propanediol; Sodium Hydroxide; Adenosine; Citric Acid Monohydrate; Myristic Acid; Tocopherol; Buddleja Davidii Leaf; Thymus Vulgaris Leaf

Cetaphil Daily Facial Moisturizer with sunscreen SPF 35

Active Ingredients

Avobenzone 2.8%
Homosalate 9.5%
Octisalate 4.8%
Octocrylene 7%

PURPOSE

Sunscreen

Uses

- helps prevent sunburn
- if used as directed with other sun protection measures (see Directions), decreases the risk of skin cancer and early skin aging caused by the sun

Warnings

For external use only

Do not use

on damaged or broken skin

When using this product

keep out of eyes. Rinse with water to remove.

Stop use and ask a doctor if

rash occurs.

Keep out of reach of children.

If swallowed, get medical help or contact a Poison Control Center right away.

Directions

- apply liberally 15 minutes before sun exposure
- use a water resistant sunscreen if swimming or sweating
- reapply at least every 2 hours
- children under 6 months of age: Ask a doctor
- Sun Protection Measures. Spending time in the sun increases your risk of skin cancer and early skin aging. To decrease this risk, regularly use a sunscreen with a Broad Spectrum SPF value of 15 or higher and other sun protection measures including:
  - limit time in the sun, especially from 10 a.m. - 2 p.m.
  - wear long-sleeved shirts, pants, hats, and sunglasses

Other information

- protect the product in this container from excessive heat and direct sun
- may stain or damage some fabrics

Inactive Ingredients

Water, Glycerin, Dipropylene Glycol, Panthenol (Vitamin B5), Ethylhexyl Methoxycrylene, lsopropyl Palmitate, Silica, Niacinamide, Cetearyl 0livate, Cetearyl Alcohol, Glyceryl Stearate, Potassium Cetyl Phosphate, Sorbitan Olivate, Tocopheryl Acetate (Vitamin E Acetate), Caprylyl Glycol, Acrylates/C10-30 Alkyl Acrylate Crosspolymer, Palmitic Acid, Ethylhexylglycerin, Stearic Acid, Leontopodium Alpinum Flower/Leaf Extract, 1,2-Hexanediol, Oryza Saliva (Rice) Lees Extract, Propanediol, Sodium Hydroxide, Adenosine, Citric Acid, Myristic Acid, Tocopherol (Vitamin E), Buddleja Davidii (Summer Lilac) Leaf Extract, Thymus Vulgaris (Thyme) Leaf Extract

Questions or comments?

1-866-735-4137

Principal Display Panel - 3 FL OZ Carton

NEW LOOK
Cetaphil®
Daily Facial
Moisturizer
AM

35 BROAD SPECTRUM
SPF 35 (UVA/UVB)
SUNSCREEN

All Skin Types

Lightweight lotion
hydrates and protects skin

Antioxidants, Vitamin B5
Oil-Free

Skin Cancer Foundation logo

3 FL OZ (88 mL)
Distributed by:
Galderma Laboratories, L.P.
Dallas, Texas 75201 USA
All trademarks are the property of their respective owners.
cetaphil.com
P56561-2